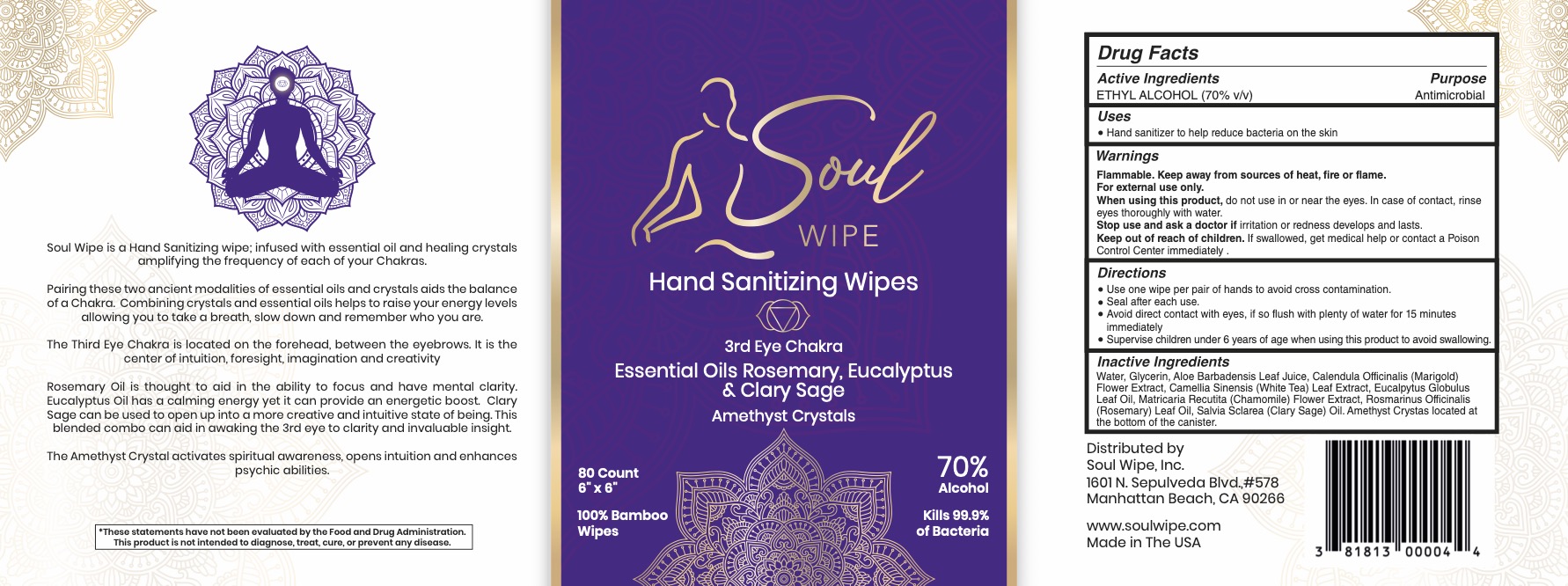 DRUG LABEL: Sole Wipe
NDC: 81813-506 | Form: GEL
Manufacturer: Soul Wipe, Inc.
Category: otc | Type: HUMAN OTC DRUG LABEL
Date: 20221127

ACTIVE INGREDIENTS: ALCOHOL 70 mL/100 mL
INACTIVE INGREDIENTS: ROSEMARY OIL 0.4 mL/100 mL; SILICON DIOXIDE; GLYCERIN 25 mL/100 mL; CHAMOMILE 0.005 mL/100 mL; CALENDULA OFFICINALIS FLOWER 0.005 mL/100 mL; GREEN TEA LEAF 0.005 mL/100 mL; ALOE VERA LEAF 0.005 mL/100 mL; WATER; CLARY SAGE OIL 0.05 mL/100 mL; EUCALYPTUS OIL 0.5 mL/100 mL

Soul Wipe
3rd Eye Chakra

STATEMENT OF IDENTITY

Hand Sanitizer Hand Wipe

ACTIVE INGREDIENT

Ethyl Alcohol 70% v/v

PURPOSE

Antiseptic

INDICATIONS AND USAGE

Hand Sanitizer to help reduce bacteria on the skin

WARNINGS

Flammable. Keep away from sources of heat, fire or flame

For external use only

When using this product, do not use in or near the eyes.

In case of contact, rinse eyes thoroughly with water

Stop use and ask a doctor if irritation or redness develops and lasts

Keep out of reach of children. If swallowed, get medical help or contact a Poison Control Center immediately

WHEN USING

Avoid contact with eyes. If so flush with plenty of water for 15 minutes immediately

Stop use and ask a doctor if irritation develops ans lasts.

Keep out of reach of children. If swallowed, get medical help or contact Poison Control Center immediately.

Directions

Use one wipe per pair of hands to avoid cross contamination

Seal after each use

Avoid contact with eyes. If so, flush with prenty of water for 15min immediately

Supervise children under 6 years of age when using this product to avoid swallowing

INACTIVE INGREDIENT

Water (aqua), Glyserin, Aloe Barbadensis leaf juice, Calendula Offincinalls (Marigold) flower extract, Camella Sinensis (white tea) leaf extract, Citrus Aurantium (Bergamont) Oil, Matricaria Recultita (Chamomile) flower extract, PogostemonCablin (Patchouli) oil, rock chrystals

STORAGE AND HANDLING

Flammable. Keep away from sources of heat, fire or flame

Seal after each use